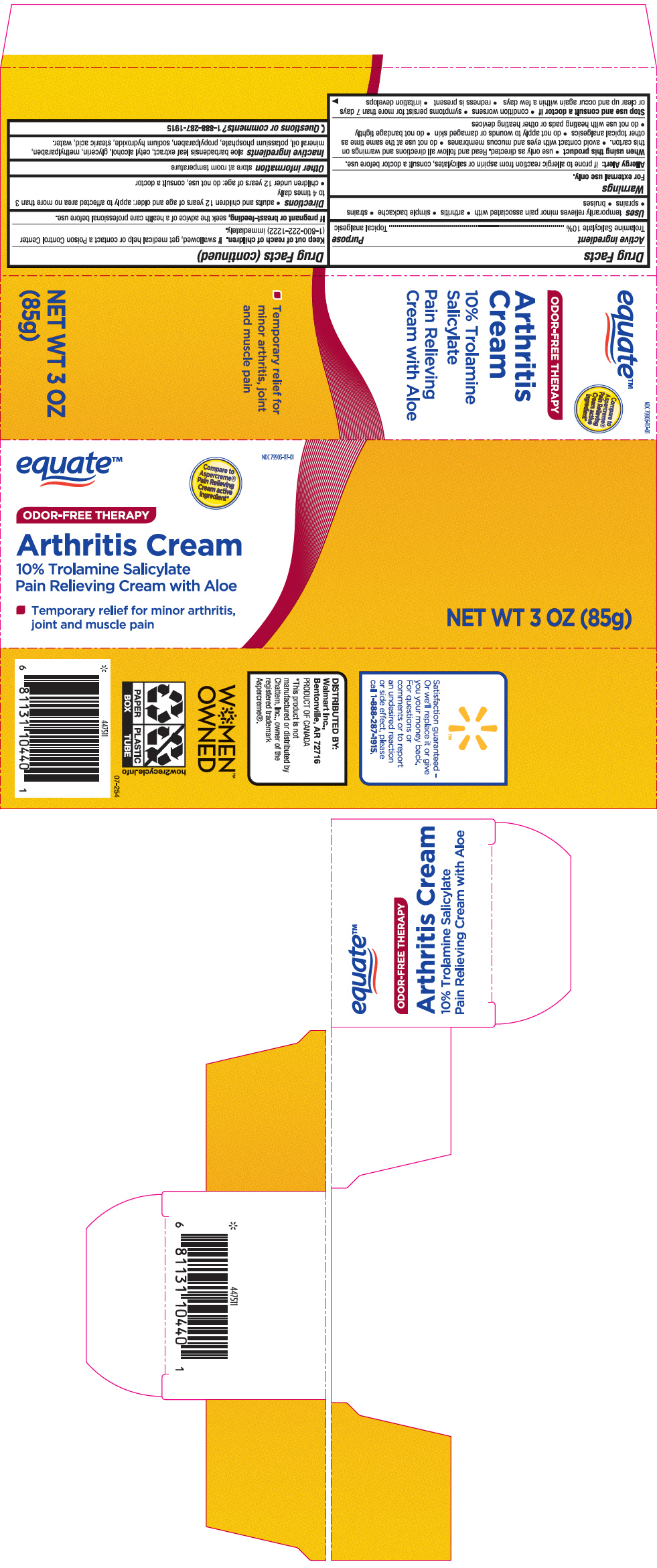 DRUG LABEL: Equate Odor-Free Therapy Arthritis
NDC: 79903-117 | Form: CREAM
Manufacturer: Wal-Mart Stores, Inc.
Category: otc | Type: HUMAN OTC DRUG LABEL
Date: 20241118

ACTIVE INGREDIENTS: Trolamine Salicylate 100 mg/1 g
INACTIVE INGREDIENTS: ALOE VERA LEAF; Cetyl Alcohol; Glycerin; Methylparaben; Mineral Oil; POTASSIUM PHOSPHATE, UNSPECIFIED FORM; Propylparaben; Sodium Hydroxide; Stearic Acid; Water

Equate™ Odor-Free Therapy Arthritis Cream
Topical Analgesic

Drug Facts

Active ingredient

Trolamine Salicylate 10%

Purpose

Topical Analgesic

Uses

temporarily relieves minor pain associated with

- arthritis
- simple backache
- strains
- sprains
- bruises

Warnings

For external use only.

Allergy Alert: if prone to allergic reaction from aspirin or salicylates, consult a doctor before use.

When using this product

- use only as directed. Read and follow all directions and warnings on this carton
- avoid contact with eyes and mucous membranes
- do not use at the same time as other topical analgesics
- do not apply to wounds or damaged skin
- do not bandage tightly
- do not use with heating pads or other heating devices

Stop use and consult a doctor if

- condition worsens
- symptoms persist for more than 7 days or clear up and occur again within a few days
- redness is present
- irritation develops

Keep out of reach of children. If swallowed, get medical help or contact a Poison Control Center (1-800-222-1222) immediately

PREGNANCY OR BREAST FEEDING

If pregnant or breast feeding, seek the advice of a health care professional before use.

Directions

- Adults and children 12 years of age and older: apply to affected area no more than 3 to 4 times daily
- children under 12 years of age: do not use, consult a doctor

Other information

store at room temperature

Inactive ingredients

aloe barbadensis leaf extract, cetyl alcohol, glycerin, methylparaben, mineral oil, potassium phosphate, propylparaben, sodium hydroxide, stearic acid, water.

Questions or comments?

1-888-287-1915

DISTRIBUTED BY:
Walmart Inc.,
Bentonville, AR 72716

PRINCIPAL DISPLAY PANEL - 85 g Tube Carton

NDC 79903-117-01

equate™

Compare to
Aspercreme®
Pain Relieving
Cream active
ingredient*

ODOR-FREE THERAPY

Arthritis Cream

10% Trolamine Salicylate
Pain Relieving Cream with Aloe

- Temporary relief for minor arthritis,
  joint and muscle pain

NET WT 3 OZ (85g)